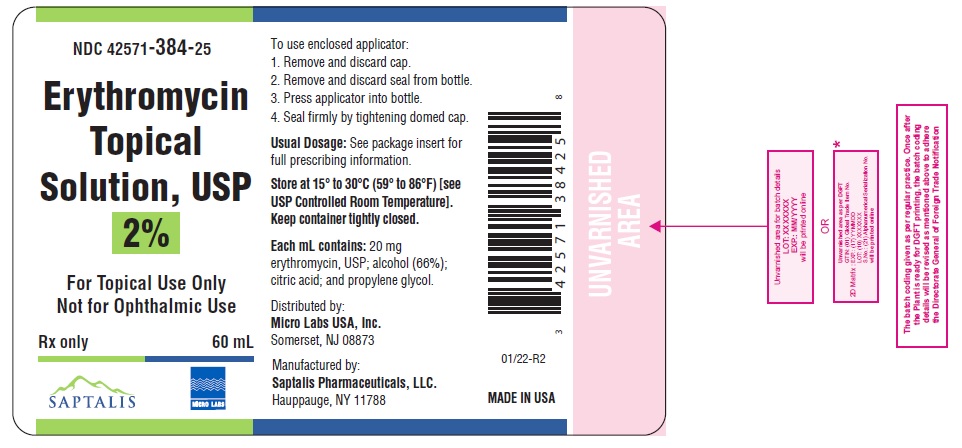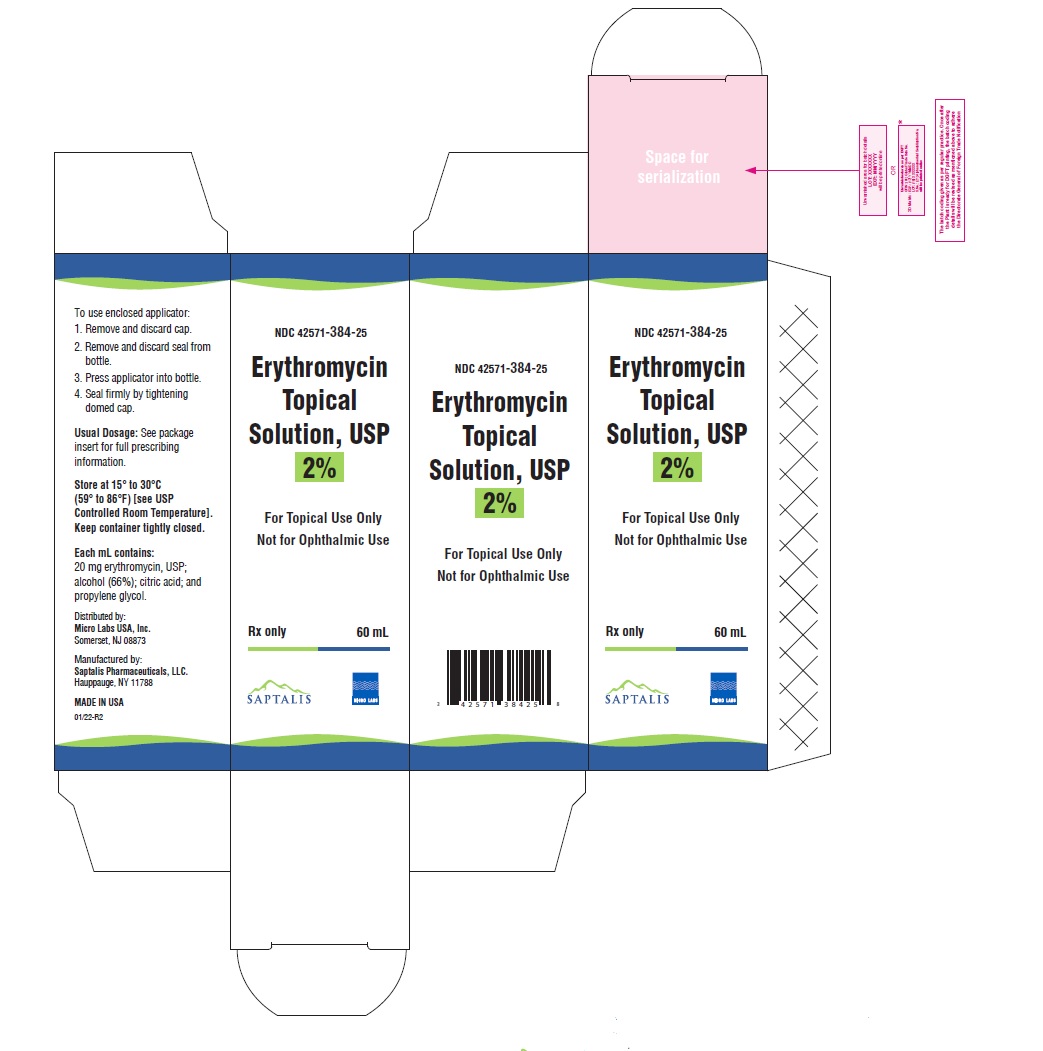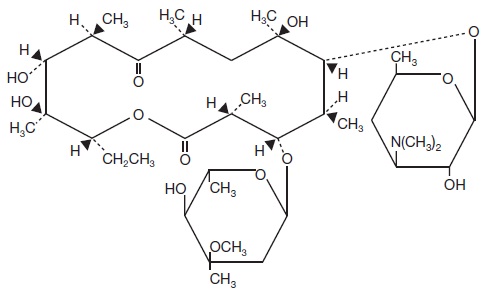 DRUG LABEL: erythromycin
NDC: 42571-384 | Form: SOLUTION
Manufacturer: MICRO LABS LIMITED
Category: prescription | Type: HUMAN PRESCRIPTION DRUG LABEL
Date: 20241227

ACTIVE INGREDIENTS: ERYTHROMYCIN 20 mg/1 mL
INACTIVE INGREDIENTS: ALCOHOL; ANHYDROUS CITRIC ACID; PROPYLENE GLYCOL

Erythromycin Topical Solution, USP 2%

For Topical Use Only

Not for Ophthalmic Use

Rx Only

DESCRIPTION

Erythromycin topical solution, USP 2% contains erythromycin, USP for topical dermatologic use. Erythromycin is a macrolide antibiotic produced from a strain of Saccaropolyspora erythraea(formerly Streptomyces erythreus). It is a base and readily forms salts with acids. Chemically, erythromycin is: (3 R*,4 S*,5 S*,6 R*,7 R*,9 R*,11 R*,12 R*,13 S*,14 R*)-4-[(2,6-Dideoxy-3- C-methyl-3- 0-methyl-α-L- ribo-hexopyranosyl)oxy]-14-ethyl-7,12,13-trihydroxy -3,5,7,9,11,13-hexamethyl-6-[[3,4,6-trideoxy-3-(dimethylamino)-ß-D- xylo-hexopyranosyl]oxy]oxacyclotetradecane-2,10-dione. It has the following structural formula:

Molecular Formula: C37H67NO13

Molecular Weight: 733.94

Erythromycin, USP is a white or slightly yellow, crystalline powder that is soluble in water, alcohol, chloroform and in ether.

Each mL of erythromycin topical solution, USP 2% contains 20 mg of erythromycin base in a vehicle consisting of alcohol (66%), citric acid, and propylene glycol.

CLINICAL PHARMACOLOGY

The exact mechanism by which erythromycin reduces lesions of acne vulgaris is not fully known; however, the effect appears to be due in part to the antibacterial activity of the drug.

Microbiology

Erythromycin acts by inhibition of protein synthesis in susceptible organisms by reversibly binding to 50S ribosomal subunits, thereby inhibiting translocation of aminoacyl transfer-RNA and inhibiting polypeptide synthesis. Antagonism has been demonstrated in vitrobetween erythromycin, lincomycin, chloramphenicol, and clindamycin.

INDICATIONS AND USAGE

Erythromycin topical solution, 2% is indicated for the topical treatment of acne vulgaris.

CONTRAINDICATIONS

Erythromycin topical solution, 2% is contraindicated in those individuals who have shown hypersensitivity to any of its components.

WARNINGS

Pseudomembranous colitis has been reported with nearly all antibacterial agents, including erythromycin, and may range in severity from mild to life-threatening. Therefore, it is important to consider this diagnosis in patients who present with diarrhea subsequent to the administration of antibacterial agents.

Treatment with antibacterial agents alters the normal flora of the colon and may permit overgrowth of clostridia. Studies indicate that a toxin produced by Clostridium difficileis one primary cause of “antibiotic-associated colitis”.

After the diagnosis of pseudomembranous colitis has been established, therapeutic measures should be initiated. Mild cases of pseudomembranous colitis usually respond to drug discontinuation alone. In moderate to severe cases, consideration should be given to management with fluids and electrolytes, protein supplementation and treatment with an antibacterial drug clinically effective against C. difficilecolitis.

PRECAUTIONS

General

For topical use only; not for ophthalmic use. Concomitant topical acne therapy should be used with caution because a possible cumulative irritancy effect may occur, especially with the use of peeling, desquamating or abrasive agents.

The use of antibiotic agents may be associated with the overgrowth of antibiotic-resistant organisms. If this occurs, discontinue use and take appropriate measures.

Avoid contact with eyes and all mucous membranes.

Information for Patients

Patients using erythromycin topical solution, 2% should receive the following information and instructions:

1. This medication is to be used as directed by the physician. It is for external use only. Avoid contact with the eyes, nose, mouth, and all mucous membranes.
2. This medication should not be used for any disorder other than that for which it was prescribed.
3. Patients should not use any other topical acne medication unless otherwise directed by their physician.
4. Patients should report to their physician any signs of local adverse reactions.

Carcinogenesis, Mutagenesis, Impairment of Fertility

No animal studies have been performed to evaluate the carcinogenic and mutagenic potential or effects on fertility of topical erythromycin. However, long-term (2 years) oral studies in rats with erythromycin ethylsuccinate and erythromycin base did not provide evidence of tumorigenicity. There was no apparent effect on male or female fertility in rats fed erythromycin (base) at levels up to 0.25% of diet.

Nursing Mothers

It is not known whether erythromycin is excreted in human milk after topical application. However, erythromycin is excreted in human milk following oral and parenteral erythromycin administration. Therefore, caution should be exercised when erythromycin is administered to a nursing woman.

Pediatric Use

Safety and effectiveness of this product in pediatric patients have not been established.

ADVERSE REACTIONS

The following local adverse reactions have been reported occasionally: peeling, dryness, itching, erythema, and oiliness. Irritation of the eyes and tenderness of the skin have also been reported with topical use of erythromycin. Generalized urticarial reactions possibly related to the use of erythromycin, which required systemic steroid therapy have been reported.

To report SUSPECTED ADVERSE REACTIONS, contact Saptalis Pharmaceuticals, LLC at 1-833-727-8254 or FDA at 1-800‑FDA‑1088 or www.fda.gov/medwatch.

DOSAGE AND ADMINISTRATION

Erythromycin topical solution, 2% should be applied over the affected areas twice a day (morning and evening) after the skin is thoroughly washed with warm water and soap and patted dry. Acne lesions on the face, neck, shoulders, chest, and back may be treated in this manner.

This medication should be applied with applicator top. If fingertips are used, wash hands after application. Drying and peeling may be controlled by reducing the frequency of applications.

HOW SUPPLIED

Erythromycin topical solution, USP 2% is available as follows:

60 mL bottle with applicator (NDC 42571-384-25)

Store at 15° to 30°C (59° to 86°F) [see USP Controlled Room Temperature]. Keep container tightly closed.

Manufactured by:
Saptalis Pharmaceuticals, LLC
Hauppauge, NY 11788

Distributed by:
Micro Labs USA, Inc.
Somerset, NJ 08873

Rev. 01/22-R2

Principal dispaly panel-Label

NDC 42571-384-25

Erythromycin Topical Solution, USP 2%

For Topical Use Only

Not for Ophthalmic Use

Rx only

60 mL

Principal dispaly panel-Carton

NDC 42571-384-25

Erythromycin Topical Solution, USP 2%

For Topical Use Only

Not for Ophthalmic Use

Rx only

60 mL